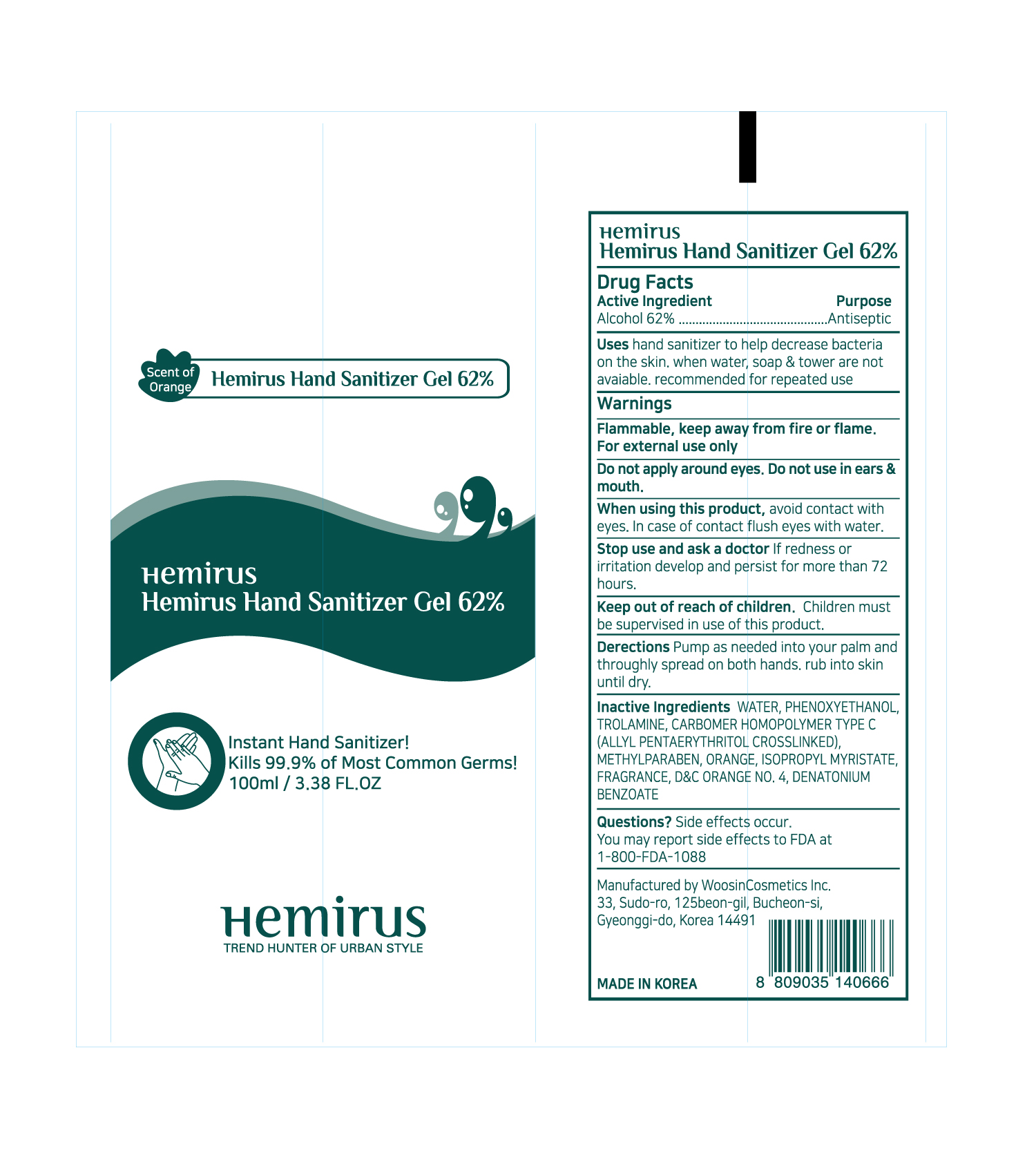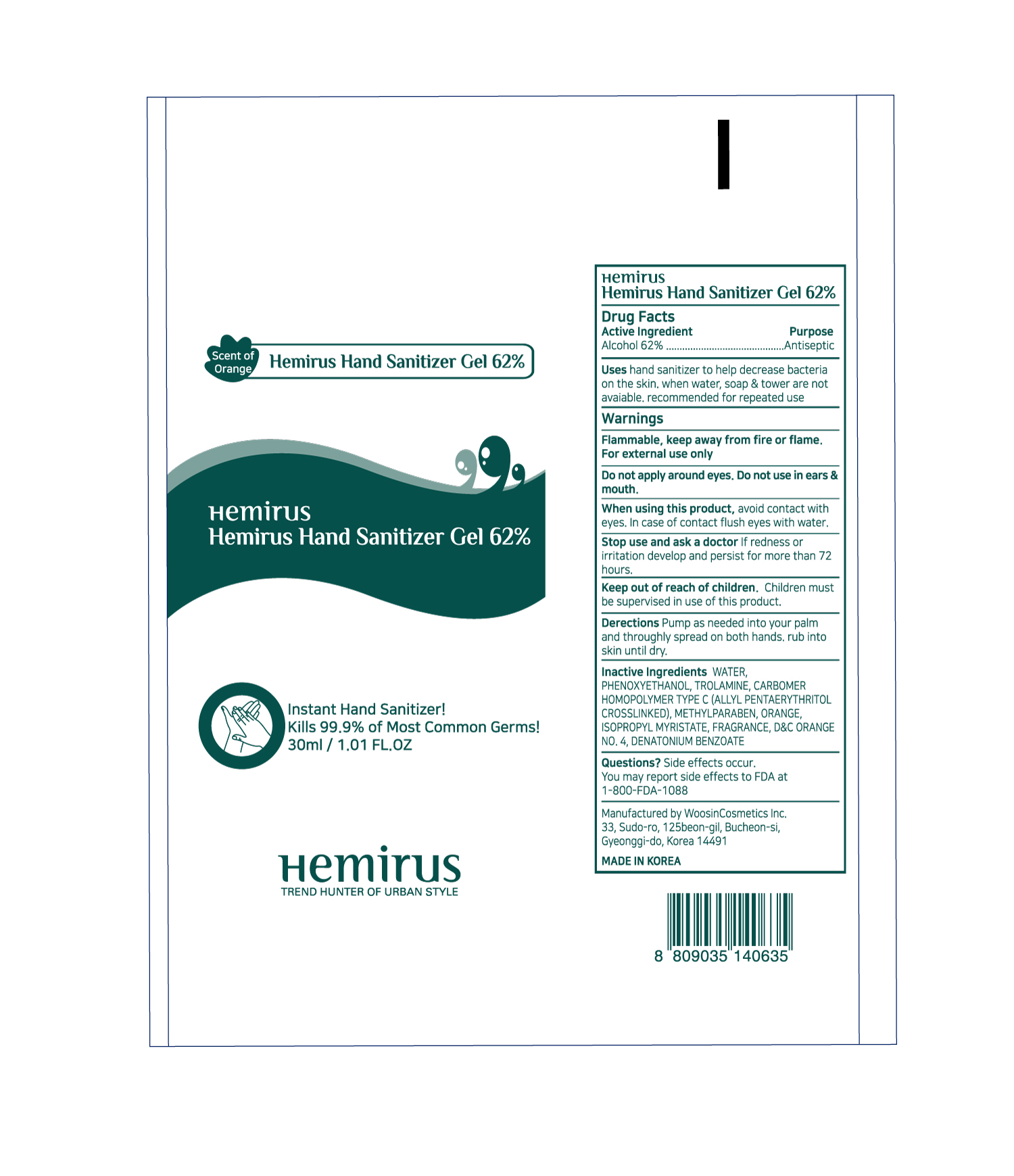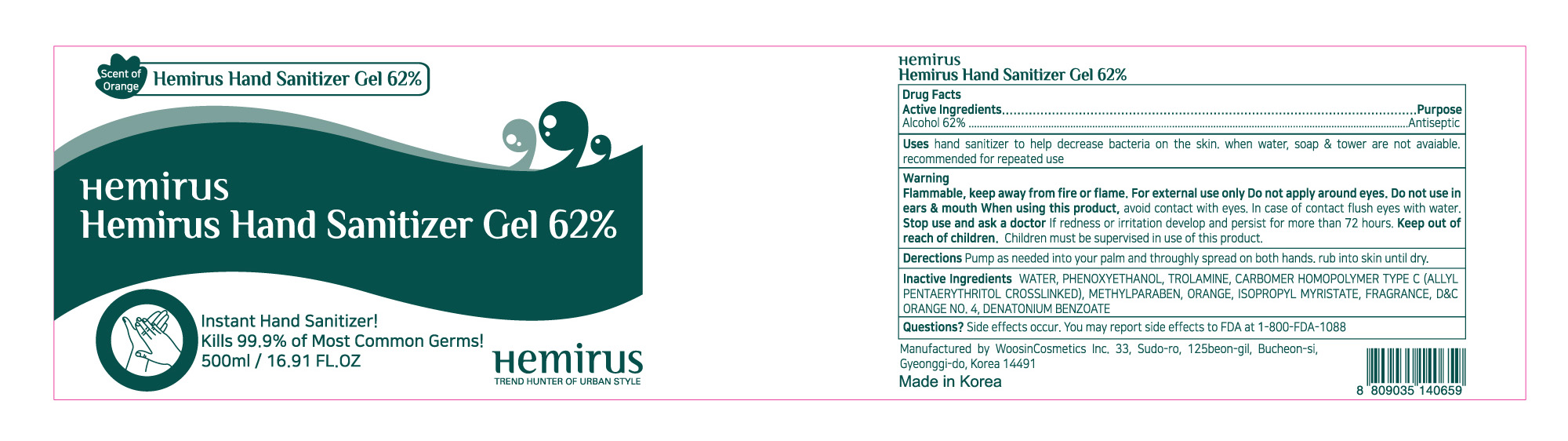 DRUG LABEL: Hemirus Hand Clinic Gel 62%
NDC: 71454-3040 | Form: GEL
Manufacturer: GC US CORPORATION
Category: otc | Type: HUMAN OTC DRUG LABEL
Date: 20200331

ACTIVE INGREDIENTS: ALCOHOL 0.62 mL/1 mL
INACTIVE INGREDIENTS: WATER; PHENOXYETHANOL; TROLAMINE; CARBOMER HOMOPOLYMER TYPE C (ALLYL PENTAERYTHRITOL CROSSLINKED); METHYLPARABEN; ORANGE; ISOPROPYL MYRISTATE; D&C ORANGE NO. 4; DENATONIUM BENZOATE

Active ingredients

Alcohol 62%

PURPOSE

Antiseptic

Uses

- hand sanitizer to help decrease bacteria on the skin.
- when water, soap & tower are not available
- recommended for repeated use

Warnings

Flammable. Keep away from fire or flame

For external use only.

Do not apply around eyes. Do not use

in ears & mouth

When using this product

avoid contact with eyes.

In case of contact flush eyes with water

Stop use and ask a doctor if

redness or irritation develop and persist for more than 72 hours.

Keep out of reach of children.

Children must be supervised in use of this product.

Directions

- pump as needed into your palms and throughly spread on both hands.
- rub into skin until dry.

Other Information

- Store at 20o C (68o to 77o F).
- may discolor fabrics.

Inactive Ingredients

Water, Phenoxyethanol, Trolamine, Carbomer homopolymer type C (Allyl pentaerythritol crosslinked)
Methylparaben, Orange, Isopropyl myristate, D&C Orange No. 4, Denatonium benzoate

Questions?

- side effects occur. You may report side effects to FDA at 1-800-FDA-1088.

ACCESSORIES

Instant Hand Sanitizer!

Kills 99.9% of Most Common Germs!

Net Wt. 16.91 fl oz. (500ml)

Manufactured by Woosincosmetics Inc.

33, Sudo-ro, 125beon-gil, Bucheon-si,
Gyeonggi-do, Korea 14491

PACKAGE LABEL

500mL NDC: 71454-3040-1

100mL NDC: 71454-3040-2

30mL NDC: 71454-3040-3